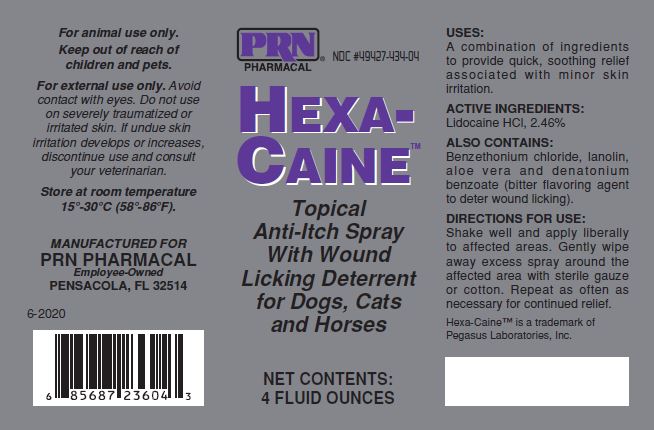 DRUG LABEL: Hexa-Caine
NDC: 49427-434 | Form: SPRAY
Manufacturer: Pegasus Laboratories, Inc.
Category: animal | Type: OTC ANIMAL DRUG LABEL
Date: 20211228

ACTIVE INGREDIENTS: LIDOCAINE HYDROCHLORIDE 24.6 mg/1 mL

INDICATIONS:

A combination of ingredients for providing quick, soothing relief associated with minor skin irritation.

CONTAINS:

Benzethonium chloride, lanolin, aloe vera and denatonium benzoate (bitter flavoring agent to deter would licking).

Storage Conditions:

Store at room temperature 15-30°C (58-86 °F)

DIRECTIONS FOR USE:

Shake well and apply liberally to affected areas. Gently wipe away excess spray around the affected area with sterile gauze or cotton. Repeat as often as necessary for continued relief.

ACTIVE INGREDIENTS:

Lidocaine HCl, 2.46%

GENERAL PRECAUTIONS

For animal use only.
Keep out of reach of children and pets.
For external use only.

Avoid contact with eyes. Do not use on severely traumatized or bleeding skin. If undue skin irritation develops or increases, discontinue use and consult your veterinarian.

Principal Display Panel:

PRN PHARMACAL

HEXA-CAINE ™

Topical Anti-Itch Spray With Wound Licking Deterrent

for Dogs, Cats, and Horses

NET CONTENTS:

4 FLUID OUNCES